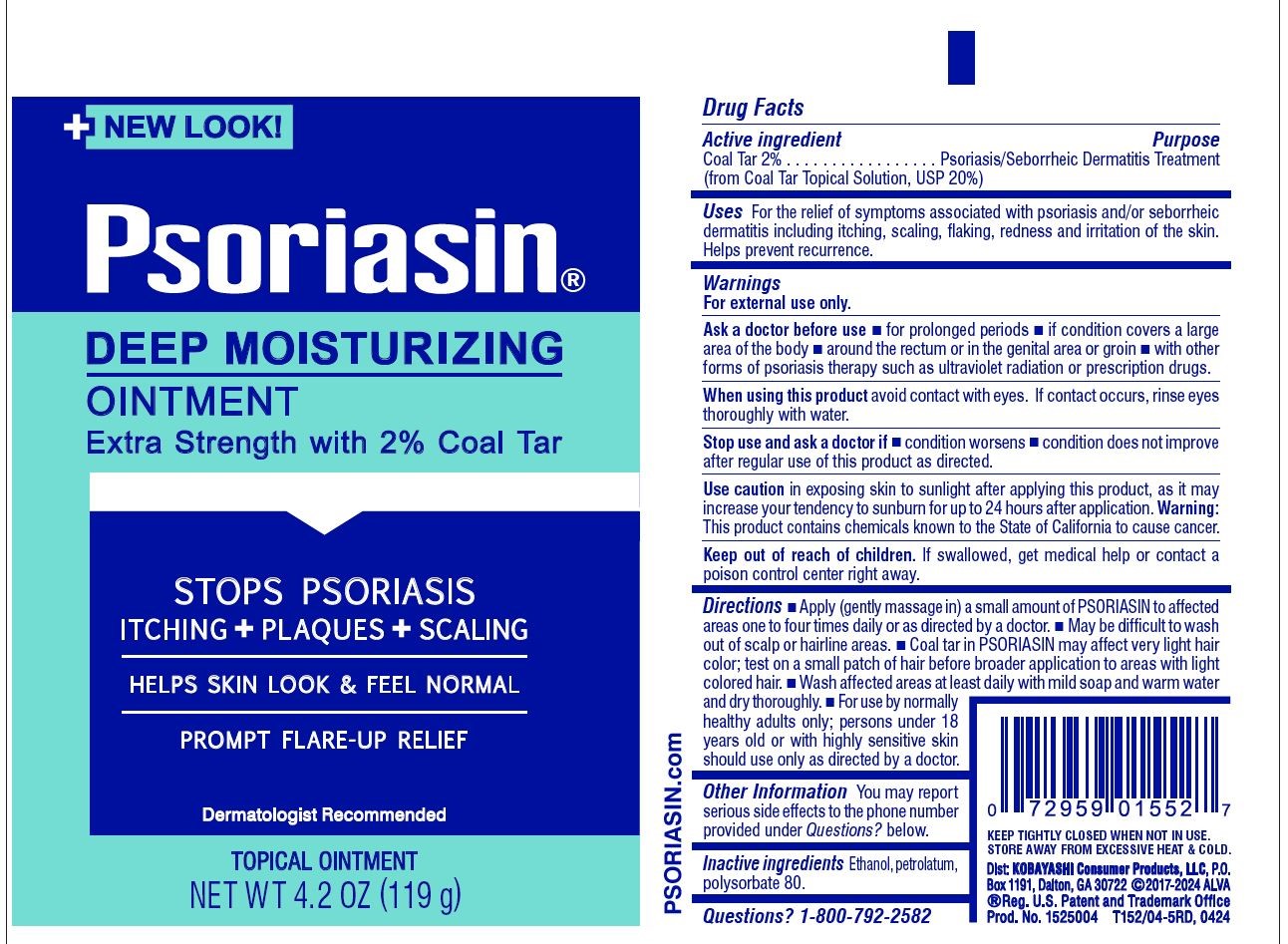 DRUG LABEL: Psoriasin
NDC: 52389-752 | Form: OINTMENT
Manufacturer: Kobayashi Healthcare International, Inc.
Category: otc | Type: HUMAN OTC DRUG LABEL
Date: 20250613

ACTIVE INGREDIENTS: COAL TAR 20 mg/1 g
INACTIVE INGREDIENTS: ALCOHOL; PETROLATUM; POLYSORBATE 80

Psoriasin Ointment

Active ingredient

Coal Tar 2% (from Coal Tar Topical Solution, USP 20%)

Purpose

Psoriasis/Seborrheic Dermatitis Treatment

Uses

For the relief of symptoms associated with psoriasis and/or seborrheic dermatitis including itching, scaling, flaking, redness and irritation of the skin. Helps prevent recurrence.

Warnings

For external use only.

Ask a doctor before use

- for prolonged periods
- if condition covers a large area of the body
- around the rectum or in the genital area or groin
- with other forms of psoriasis therapy such as ultraviolet radiation or prescription drugs.

When using this product avoid contact with eyes. If contact occurs, rinse eyes thoroughly with water.

Stop use and ask a doctor if

- condition worsens
- condition does not improve after regular use of this product as directed.

Use caution in exposing skin to sunlight after applying this product, as it may increase your tendency to sunburn for up to 24 hours after application.

Warning: This product contains chemicals known to the State of California to cause cancer.

Keep out of reach of children. If swallowed, get medical help or contact a poison control center right away.

Directions

- Apply (gently massage in) a small amount of Psoriasin to affected areas one to four times daily or as directed by a doctor.
- May be difficult to wash out of scalp or hairline areas.
- Coal tar in Psoriasin may affect very light hair color; test first on a small patch of hair before broader application to areas with light colored hair.
- Wash affected areas at least daily with mild soap and warm water and dry thoroughly.
- For use by normally healthy adults only; persons under 18 years old or with highly sensitive or allergic skin should use only as directed by a doctor.

Other information

You may report serious side effects to the phone number provided under Questions? below.

Inactive ingredients

Ethanol, petrolatum, polysorbate 80.

Questions?

1-800-792-2582